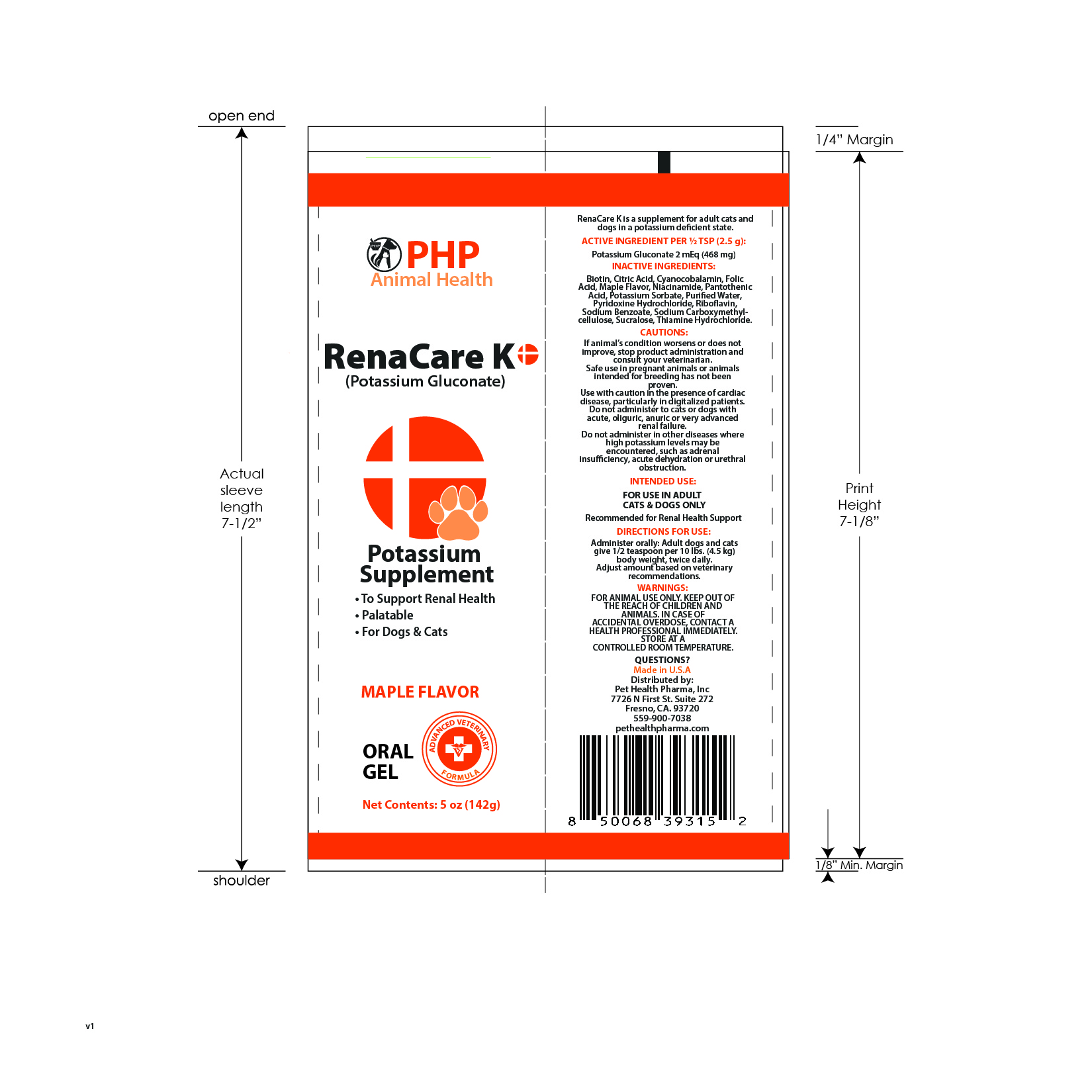 DRUG LABEL: RENACARE K
NDC: 86176-305 | Form: GEL
Manufacturer: Pet Health Pharma, LLC
Category: animal | Type: OTC ANIMAL DRUG LABEL
Date: 20250826

ACTIVE INGREDIENTS: Potassium Gluconate 468 mg/1 g
INACTIVE INGREDIENTS: BIOTIN; CITRIC ACID MONOHYDRATE; CYANOCOBALAMIN; FOLIC ACID; NIACINAMIDE; PANTOTHENIC ACID; POTASSIUM SORBATE; WATER; PYRIDOXINE HYDROCHLORIDE; RIBOFLAVIN; SODIUM BENZOATE; CARBOXYMETHYLCELLULOSE SODIUM; SUCRALOSE; THIAMINE HYDROCHLORIDE

RENACARE K Potassium Supplement for Dogs and Cats

Product Facts

Potassium Gluconate ............2 mEq (468 mg) per 2.5g

INACTIVE INGREDIENTS:

Biotin, Citric Acid, Cyanocobalamin, Folic Acid, Maple Flavor, Niacinamide, Pantothenic Acid, Potassium Sorbate, Purified Water, Pyridoxine Hydrochloride, Riboflavin, Sodium Benzoate, Sodium Carboxymethylcellulose, Sucralose, Thiamine Hydrochloride.

CAUTIONS:

If animal's condition worsens or does not improve, stop product administration and consult your veterinarian.

Safe use in pregnant animals or animals intended for breeding has not been proven.

Use with caution in the presence of cardiac disease, particularly in digitalized patients.

Do not administer to cats or dogs with acute, oliguric, anuric or very advanced renal failure.

Do not administer in other diseases where high potassium levels may be encountered, such as adrenal insufficiency, acute dehydration or urethral obstruction.

INTENDED USE:

FOR USE IN ADULT CATS & DOGS ONLY

Recommended for Renal Health Support

DIRECTIONS FOR USE:

Administer orally: Adult dogs and cats give 1/2 teaspoon per 10 lbs. (4.5 kg) body weight, twice daily.

Adjust amount based on veterinary recommendations.

WARNINGS:

FOR ANIMAL USE ONLY. KEEP OUT OF THE REACH OF CHILDREN AND ANIMALS. IN CASE OF ACCIDENTAL OVERDOSE, CONTACT A HEALTH PROFESSIONAL IMMEDIATELY. STORE AT A CONTROLLED ROOM TEMPERATURE.

QUESTIONS:

Made in U.S.A

Distributed by:

Pet Health Pharma, Inc.

7726 N First St. Suite 272

Fresno, CA 93720

559-900-7038

pethealthpharma.com